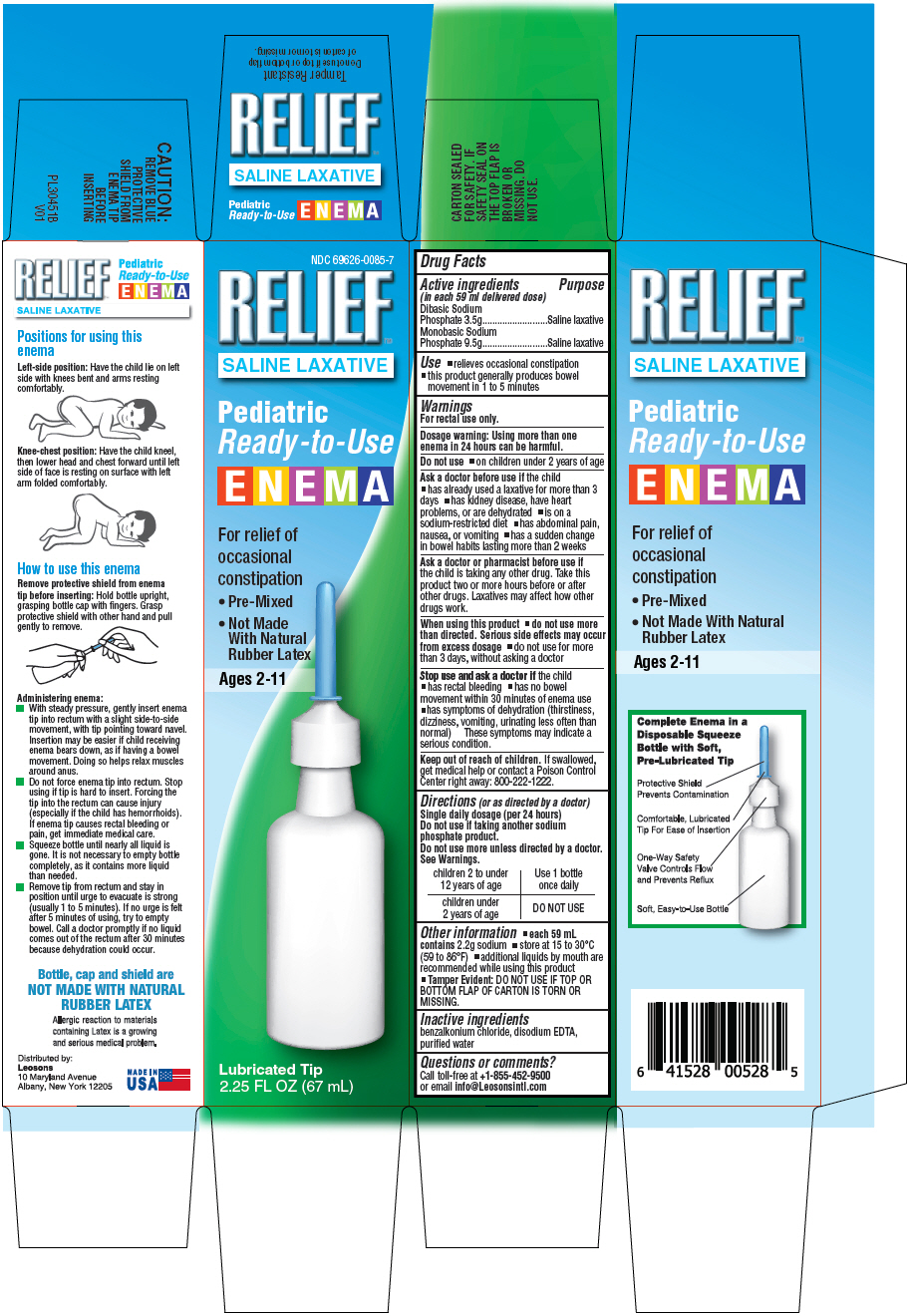 DRUG LABEL: REFLIEF SALINE LAXATIVE PEDIATRIC READY TO USE
NDC: 69626-0085 | Form: ENEMA
Manufacturer: Leosons Overseas Corp
Category: otc | Type: HUMAN OTC DRUG LABEL
Date: 20241119

ACTIVE INGREDIENTS: SODIUM PHOSPHATE, DIBASIC, UNSPECIFIED FORM 3.5 g/59 mL; SODIUM PHOSPHATE, MONOBASIC, UNSPECIFIED FORM 9.5 g/59 mL
INACTIVE INGREDIENTS: BENZALKONIUM CHLORIDE; EDETATE DISODIUM; WATER

Relief Pediatric Enema (NaturePlex)

Drug Facts

Active ingredients & Purpose

PURPOSE

Active ingredients (in each 59 ml delivered dose) | Purpose
Dibasic Sodium Phosphate 3.5g..... | Saline laxative
Monobasic Sodium Phosphate 9.5g..... | Saline laxative

Uses

- relieves occasional constipation
- this product generally produces bowel movement in 1 to 5 minutes

Warnings

For rectal use only.

Dosage warning:

Using more than one enema in 24 hours can be harmful.

Do not use

- on children under 2 years of age

Ask a doctor before use if the child

- has already used a laxative for more than 3 days
- has kidney disease, have heart problems, or are dehydrated
- is on a sodium-restricted diet
- has abdominal pain, nausea, or vomiting
- has a sudden change in bowel habits lasting more than 2 weeks

Ask a doctor or pharmacist before use if

the child is taking any other drug. Take this product two or more hours before or after other drugs. Laxatives may affect how other drugs work.

When using this product

- do not use more than directed. Serious side effects may occur from excess dosage
- do not use for more than 3 days, without asking a doctor

Stop use and ask a doctor if the child

- has rectal bleeding
- has no bowel movement within 30 minutes of enema use
- has symptoms of dehydration (thirstiness, dizziness, vomiting, urinating less often than normal). These symptoms may indicate a serious condition.

Keep out of reach of children.

If swallowed, get medical help or contact a Poison Control Center right away: 800-222-1222.

Directions (or as directed by a doctor)

- Single daily dosage (per 24 hours)
- Do not use if taking another sodium phosphate product.
- Do not use more unless directed by a doctor. See Warnings.

children 2 to under 12 years of age | Use 1 bottle once daily
children under 2 years of age | DO NOT USE

Other information

- each 59 mL contains 2.2g sodium
- store at 15 to 30°C (59 to 86°F)
- additional liquids by mouth are recommended while using this product
- Tamper Evident: DO NOT USE IF TOP OR BOTTOM FLAP OF CARTON IS TORN OR MISSING.

Inactive ingredients

benzalkonium chloride, disodium EDTA, purified water

Questions or comments?

Call toll-free at +1-855-452-9500 or email info@Leosonsintl.com

Distributed by:

Leosons
10 Maryland Avenue
Albany, New York 12205

PRINCIPAL DISPLAY PANEL

NDC 69626-0085-7

RELIEF™
SALINE LAXATIVE

Pediatric
Ready-to-Use

ENEMA

For relief of occasional constipation

- Pre-Mixed
- Not Made With Natural Rubber Latex

Ages 2-11

Lubricated Tip
2.25 FL OZ (67 mL)